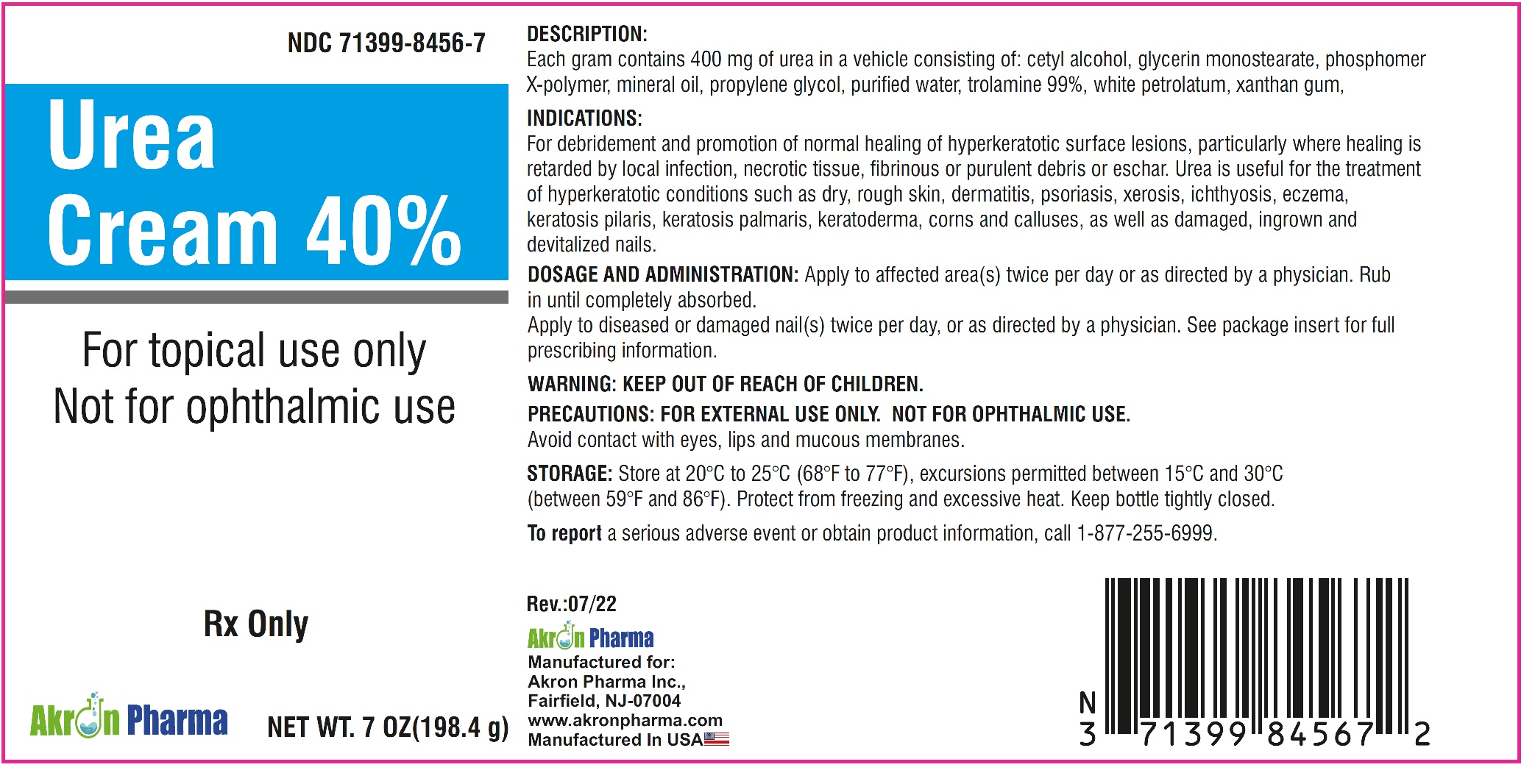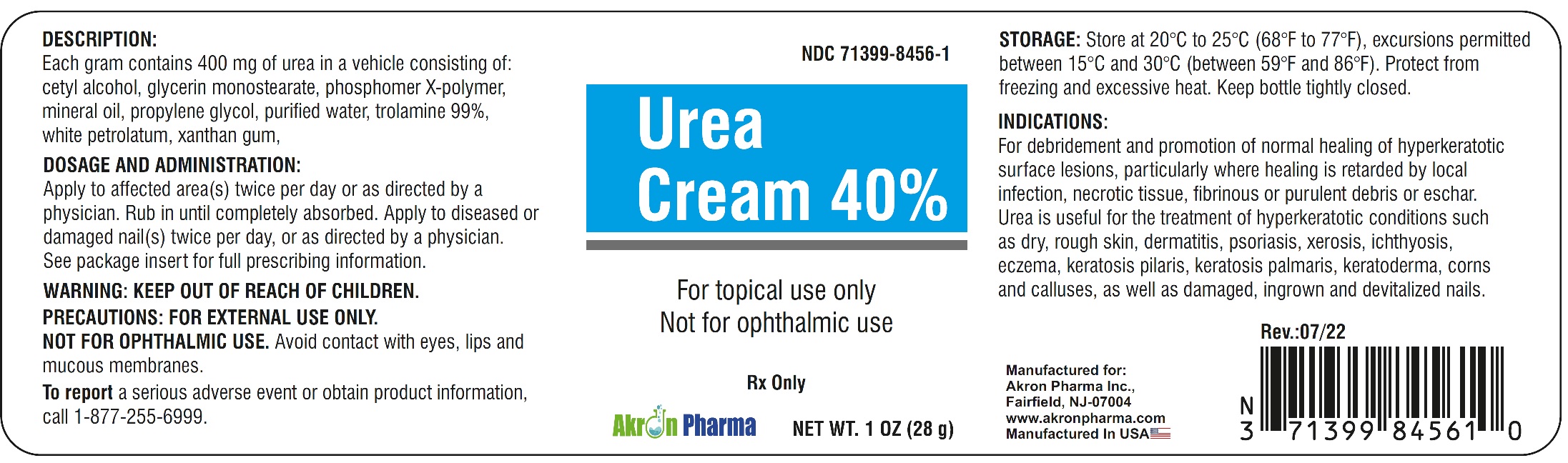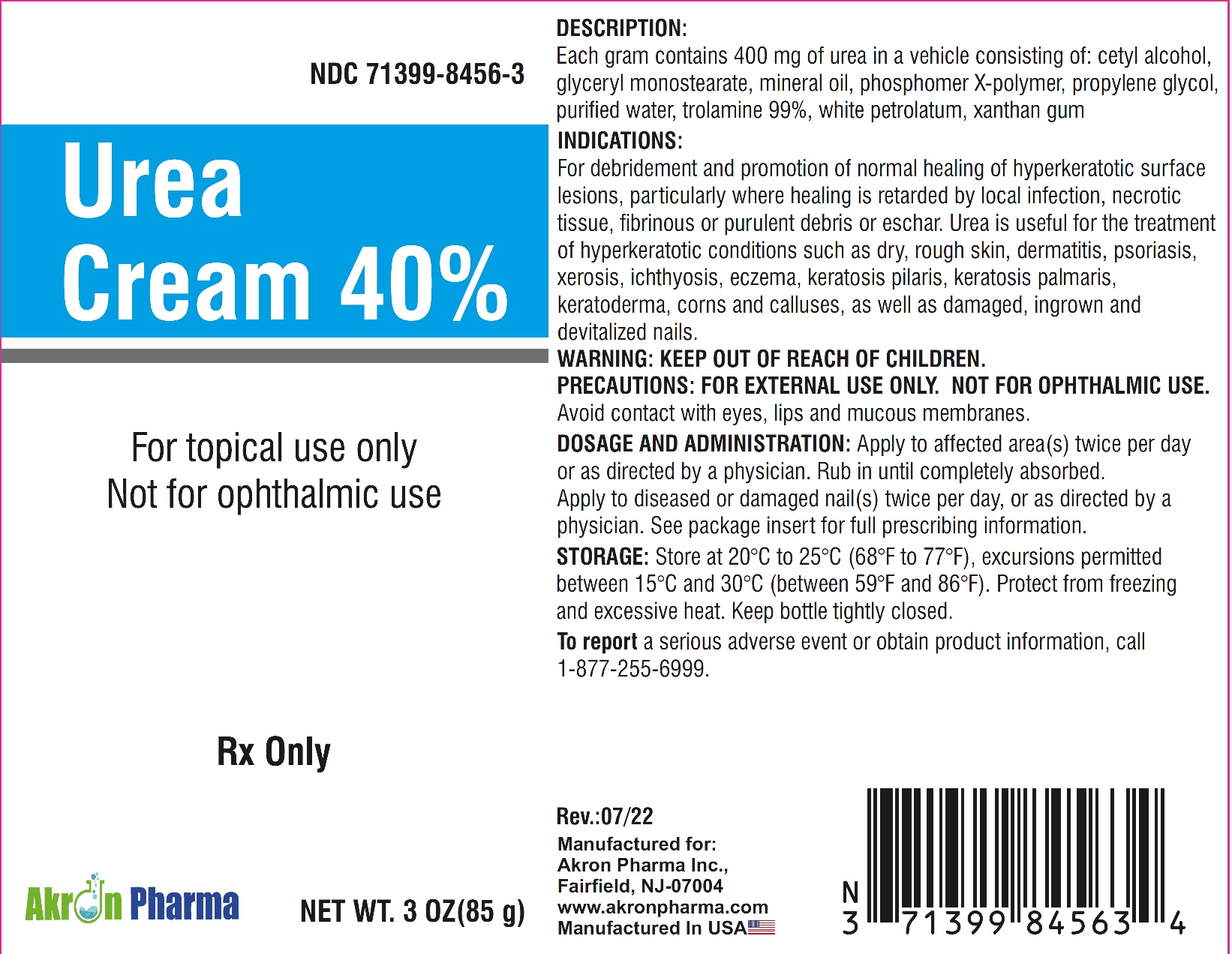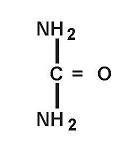 DRUG LABEL: Urea Cream 40%
NDC: 71399-8456 | Form: CREAM
Manufacturer: Akron Pharma Inc.
Category: prescription | Type: HUMAN PRESCRIPTION DRUG LABEL
Date: 20240925

ACTIVE INGREDIENTS: UREA 400 mg/1 g
INACTIVE INGREDIENTS: CETYL ALCOHOL; GLYCERYL MONOSTEARATE; CARBOMER HOMOPOLYMER TYPE C (ALLYL PENTAERYTHRITOL CROSSLINKED); MINERAL OIL; PROPYLENE GLYCOL; WATER; TROLAMINE; WHITE PETROLATUM; XANTHAN GUM

Urea Cream 40%

Urea 40%

Rx Only

For topical use only.

Not for ophthalmic use.

Description

Each gram contains 400 mg of urea in a vehicle consisting of:
cetyl alcohol, glycerin monostearate, phosphomer X-polymer, mineral oil, propylene glycol, purified water, trolamine 99%, white petrolatum, xanthan gum.

Clinical Pharmacology

Urea gently dissolves the intracellular matrix which results in loosening of the horny layer of the skin and shedding of scaly skin at regular intervals, thereby softening hyperkeratotic areas of the skin.

Pharmacokinetics

The mechanism of action of topically applied urea is not yet known.

Indications and Usage

For debridement and promotion of normal healing of hyperkeratotic surface lesions, particularly where healing is retarded by local infection, necrotic tissue, fibrinous or purulent debris or eshar. Urea is useful for the treatment of hyperkeratotic conditions such as dry, rough skin, dermatitis, psoriasis, xerosis, ichthyosis, eczema, keratosis pilaris, keratosis palmaris, keratoderma, corns and calluses, as well as damaged, ingrown and devitalized nails.

Contraindications

Known hypersensitivity to any of the listed ingredients.

Warnings

For topical use only. Avoid contact with eyes, lips or mucous membranes.

KEEP OUT OF REACH OF CHILDREN.

Precautions

FOR EXTERNAL USE ONLY.
NOT FOR OPHTHALMIC USE. Avoid contact with eyes, lips and mucous membranes.

PREGNANCY

PREGNANACY

Pregnancy Category B. Animal reproduction studies have revealed no evidence of harm to the fetus, however, there are no adequate and well-controlled studies in pregnant women. Because animal reproductive studies are not always predictive of human response, Urea 40% should be given to a pregnant woman only if clearly needed.

NURSING MOTHERS

It is not known whether or not this drug is excreted in human milk. Because many drugs are excreted in human milk, caution should be exercised when Urea 40% is administered to a nursing woman.

Adverse Reactions

Transient stinging, burning, itching or irritation may occur and normally disappear upon discontinuing the medication.

To report a serious adverse event or obtain product information, call 1-877-255-6999.

Dosage and Administration

Apply Urea 40% to affected skin twice per day, or as directed by your physician. Rub in until completely absorbed.

Apply to diseased or damaged nail(s) twice per day, or as directed by a physician.

All prescription substitutions and/or recommendations using this product shall be made subject to state and federal statutes as applicable. Please note: this is not an Orange Book product and has not been subjected to FDA therapeutic equivalency or other equivalency testing. No representation is made as to generic status or bioequivalency. Each person recommending a prescription substitution using this product shall make such recommendations based on each person's professional opinion and knowledge, upon evaluation of the active ingredients, excipients, inactive ingredients and chemical information provided herein.

How Supplied

Urea 40% Cream 1 oz.(28.35 g): NDC 71399-8456-1; Urea 40% Cream 3 oz.(85 g): NDC NDC 71399-8456-3; Urea 40% Cream 7 oz.(198.45 g): NDC NDC 71399-8456-7

Store at 20°C to 25°C (68°F to 77°F), excursions permitted between 15°C and 30°C (between 59°F and 86°F). Protect from freezing and excessive heat. Keep bottle tightly closed.

Manufactured for:
Akron Pharma Inc.,
Fairfield, NJ-07004
www.akronpharma.com

Manufactured In USA